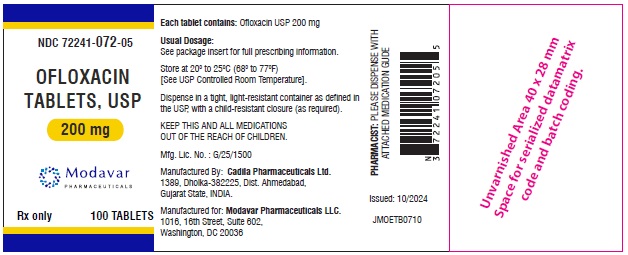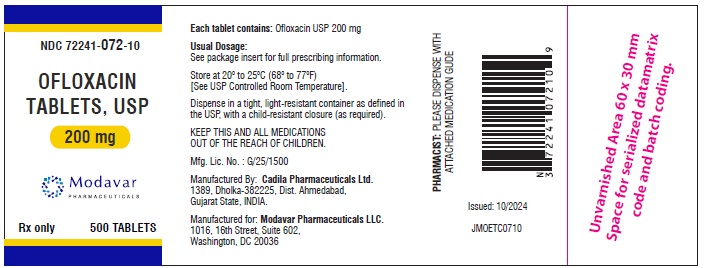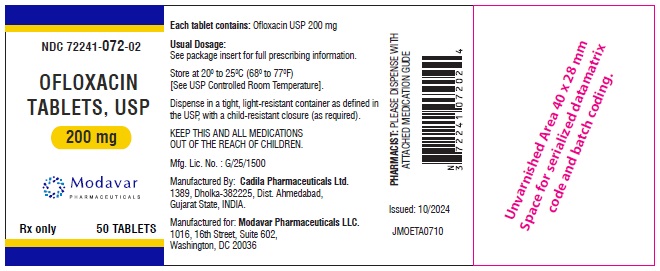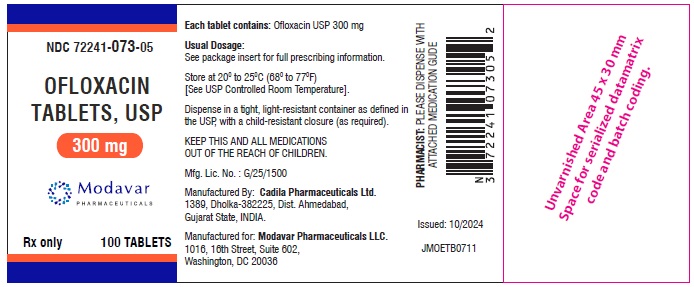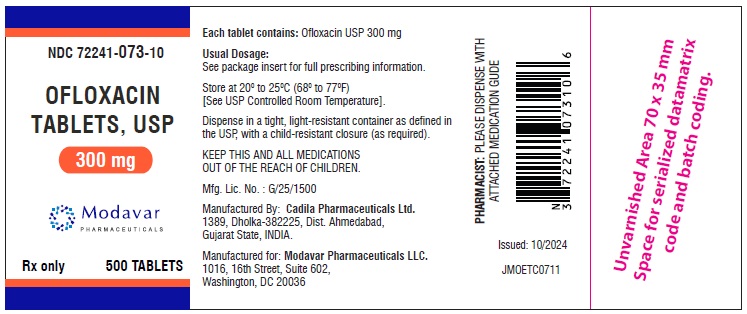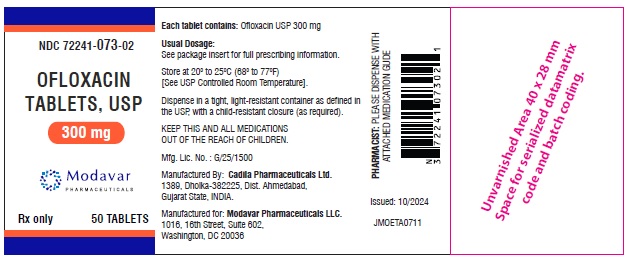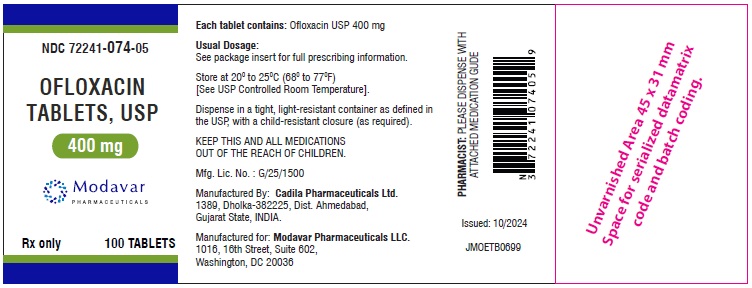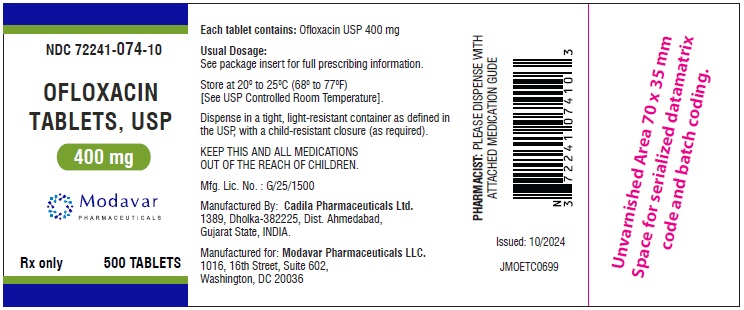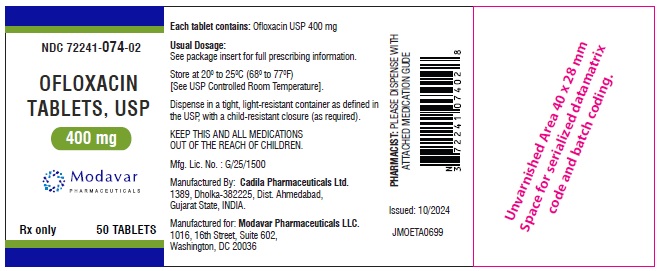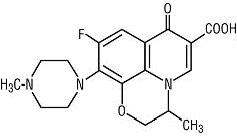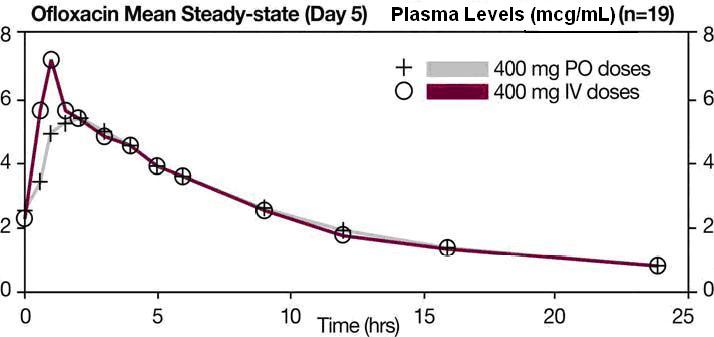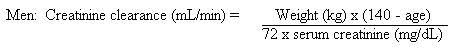 DRUG LABEL: OFLOXACIN
NDC: 72241-072 | Form: TABLET, FILM COATED
Manufacturer: Modavar Pharmaceuticals LLC
Category: prescription | Type: Human Prescription Drug Label
Date: 20241009

ACTIVE INGREDIENTS: OFLOXACIN 200 mg/1 1
INACTIVE INGREDIENTS: LACTOSE MONOHYDRATE; STARCH, CORN; HYPROMELLOSE 2910 (5 MPA.S); SODIUM STARCH GLYCOLATE TYPE A POTATO; TALC; MAGNESIUM STEARATE; POLYETHYLENE GLYCOL 400; TITANIUM DIOXIDE; FERRIC OXIDE YELLOW; HYPROMELLOSES; FD&C BLUE NO. 1; ISOPROPYL ALCOHOL; BUTYL ALCOHOL; PROPYLENE GLYCOL; SHELLAC

Rx only

WARNING

SERIOUS ADVERSE REACTIONS INCLUDING TENDINITIS, TENDON RUPTURE, PERIPHERAL NEUROPATHY, CENTRAL NERVOUS SYSTEM EFFECTS AND EXACERBATION OF MYASTHENIA GRAVIS

Fluoroquinolones, including ofloxacin, have been associated with disabling and potentially irreversible serious adverse reactions that have occurred together, including:
• Tendinitis and tendon rupture
• Peripheral neuropathy
• Central nervous system effects (see WARNINGS).
Discontinue ofloxacin immediately and avoid the use of fluoroquinolones, including ofloxacin, in patients who experience any of these serious adverse reactions (see WARNINGS).
• Fluoroquinolones, including ofloxacin, may exacerbate muscle weakness in persons with myasthenia gravis. Avoid ofloxacin in patients with a known history of myasthenia gravis (See WARNINGS).
•Because fluoroquinolones, including ofloxacin, have been associated with serious adverse reactions (see WARNINGS), reserve ofloxacin for use in patients who have no alternative treatment options for the following indications:
o Acute exacerbation of chronic bronchitis
o Uncomplicated cystitis (see INDICATIONS and USAGE)

To reduce the development of drug-resistant bacteria and maintain the effectiveness of ofloxacin tablets and other antibacterial drugs, ofloxacin tablets should be used only to treat or prevent infections that are proven or strongly suspected to be caused by bacteria.

DESCRIPTION

Ofloxacin tablets are a synthetic broad-spectrum antimicrobial agent for oral administration. Chemically, ofloxacin, USP, a fluorinated carboxyquinolone, is the racemate, (±)-9-fluoro-2,3-dihydro-3-methyl-10-(4-methyl-1-piperazinyl)-7-oxo-7H-pyrido[1,2,3-de]-1,4-benzoxazine-6-carboxylic acid. The chemical structure is:

C18H20FN3O4 M.W. 361.4

Ofloxacin, USP is an off-white to pale yellow crystalline powder. The molecule exists as a zwitterion at the pH conditions in the small intestine. The relative solubility characteristics of ofloxacin USP at room temperature, as defined by USP nomenclature, indicate that ofloxacin, USP is considered to be soluble in aqueous solutions with pH between 2 and 5. It is sparingly to slightly soluble in aqueous solutions with pH 7 (solubility falls to 4 mg/mL) and freely soluble in aqueous solutions with pH above 9. Ofloxacin USP has the potential to form stable coordination compounds with many metal ions. This in vitro chelation potential has the following formation order: Fe^+3> Al^+3> Cu ^+2> Ni ^+2> Pb^+2> Zn^+2> Mg^+2> Ca ^+2> Ba ^+2

Ofloxacin Tablets, USP contain the following inactive ingredients: lactose monohydrate, pregelatinized maize starch, hydroxy propyl methyl cellulose, talc, magnesium stearate, polyethylene glycol, sodium starch glycolate, and titanium dioxide. Additionally, the 200 mg and 400 mg tablets contain iron oxide yellow.

The imprinting ink for 200 mg, 300 mg and 400 mg strength contains FD&C blue #1, isopropyl alcohol, Nbutyl alcohol, propylene glycol, shellac and titanium dioxide.

CLINICAL PHARMACOLOGY

Following oral administration, the bioavailability of ofloxacin in the tablet formulation is approximately 98%. Maximum serum concentrations are achieved one to two hours after an oral dose. Absorption of ofloxacin after single or multiple doses of 200 to 400 mg is predictable, and the amount of drug absorbed increases proportionately with the dose. Ofloxacin has biphasic elimination. Following multiple oral doses at steady-state administration, the half-lives are approximately 4 to 5 hours and 20 to 25 hours. However, the longer half-life represents less than 5% of the total AUC. Accumulation at steady-state can be estimated using a half-life of 9 hours. The total clearance and volume of distribution are approximately similar after single or multiple doses. Elimination is mainly by renal excretion. The following are mean peak serum concentrations in healthy 70 to 80 kg male volunteers after single oral doses of 200, 300, or 400 mg of ofloxacin or after multiple oral doses of 400 mg.

Oral Dose | Serum Concentration 2 Hours After Admin. (mcg/mL) | Area Under the Curve (AUC(0 to ∞))(mcg•h/mL)
200 mg single dose | 1.5 | 14.1
300 mg single dose | 2.4 | 21.2
400 mg single dose | 2.9 | 31.4
400 mg steady-state | 4.6 | 61.0

Steady-state concentrations were attained after four oral doses, and the area under the curve (AUC) was approximately 40% higher than the AUC after single doses. Therefore, after multiple-dose administration of 200 mg and 300 mg doses, peak serum levels of 2.2 mcg/mL and 3.6 mcg/mL, respectively, are predicted at steady-state.

In vitro, approximately 32% of the drug in plasma is protein bound.

The single dose and steady-state plasma profiles of ofloxacin injection were comparable in extent of exposure (AUC) to those of ofloxacin tablets when the injectable and tablet formulations of ofloxacin were administered in equal doses (mg/mg) to the same group of subjects. The mean steady-state AUC(0 to 12) attained after the intravenous administration of 400 mg over 60 min was 43.5 mcg•h/mL; the mean steady-state AUC(0 to 12) attained after the oral administration of 400 mg was 41.2 mcg•h/mL (two one-sided t-test, 90% confidence interval was 103 to 109). (see following chart).

Between 0 and 6 h following the administration of a single 200 mg oral dose of ofloxacin to 12 healthy volunteers, the average urine ofloxacin concentration was approximately 220 mcg/mL. Between 12 and 24 hours after administration, the average urine ofloxacin level was approximately 34 mcg/mL.
Following oral administration of recommended therapeutic doses, ofloxacin has been detected in blister fluid, cervix, lung tissue, ovary, prostatic fluid, prostatic tissue, skin, and sputum. The mean concentration of ofloxacin in each of these various body fluids and tissues after one or more doses was 0.8 to 1.5 times the concurrent plasma level. Inadequate data are presently available on the distribution or levels of ofloxacin in the cerebrospinal fluid or brain tissue.
Ofloxacin has a pyridobenzoxazine ring that appears to decrease the extent of parent compound metabolism. Between 65% and 80% of an administered oral dose of ofloxacin is excreted unchanged via the kidneys within 48 hours of dosing. Studies indicate that less than 5% of an administered dose is recovered in the urine as the desmethyl or N-oxide metabolites. Four to eight percent of an ofloxacin dose is excreted in the feces. This indicates a small degree of biliary excretion of ofloxacin.
The administration of ofloxacin tablets with food does not affect the Cmax and AUC∞ of the drug, but Tmax is prolonged.
Clearance of ofloxacin is reduced in patients with impaired renal function (creatinine clearance rate < 50 mL/min), and dosage adjustment is necessary. (see PRECAUTIONS, General and DOSAGE AND ADMINISTRATION).
Following oral administration to healthy elderly subjects (65 to 81 years of age), maximum plasma concentrations are usually achieved one to two hours after single and multiple twice-daily doses, indicating that the rate of oral absorption is unaffected by age or gender. Mean peak plasma concentrations in elderly subjects were 9 to 21% higher than those observed in younger subjects. Gender differences in the pharmacokinetic properties of elderly subjects have been observed. Peak plasma concentrations were 114% and 54% higher in elderly females compared to elderly males following single and multiple twice-daily doses. [This interpretation was based on study results collected from two separate studies.] Plasma concentrations increase dose-dependently with the increase in doses after single oral dose and at steady state. No differences were observed in the volume of distribution values between elderly and younger subjects. As in younger subjects, elimination is mainly by renal excretion as unchanged drug in elderly subjects, although less drug is recovered from renal excretion in elderly subjects. Consistent with younger subjects, less than 5% of an administered dose was recovered in the urine as the desmethyl and N-oxide metabolites in the elderly. A longer plasma half-life of approximately 6.4 to 7.4 hours was observed in elderly subjects, compared with 4 to 5 hours for young subjects. Slower elimination of ofloxacin is observed in elderly subjects as compared with younger subjects which may be attributable to the reduced renal function and renal clearance observed in the elderly subjects. Because ofloxacin is known to be substantially excreted by the kidney, and elderly patients are more likely to have decreased renal function, dosage adjustment is necessary for elderly patients with impaired renal function as recommended for all patients. (see PRECAUTIONS, General and DOSAGE AND ADMINISTRATION).

MICROBIOLOGY

Ofloxacin is a quinolone antimicrobial agent. The mechanism of action of ofloxacin and other fluoroquinolone antimicrobials involves inhibition of bacterial topoisomerase IV and DNA gyrase (both of which are type II topoisomerases), enzymes required for DNA replication, transcription, repair and recombination.

Ofloxacin has in vitro activity against a wide range of gram-negative and gram-positive microorganisms. Ofloxacin is often bactericidal at concentrations equal to or slightly greater than inhibitory concentrations.

Fluoroquinolones, including ofloxacin, differ in chemical structure and mode of action from aminoglycosides, macrolides and β-lactam antibiotics, including penicillins. Fluoroquinolones may, therefore, be active against bacteria resistant to these antimicrobials.

Resistance to ofloxacin due to spontaneous mutation in vitro is a rare occurrence (range: 10^-9 to 10^-11). Although cross-resistance has been observed between ofloxacin and some other fluoroquinolones, some microorganisms resistant to other fluoroquinolones may be susceptible to ofloxacin.

Ofloxacin has been shown to be active against most strains of the following microorganisms both in vitro and in clinical infections as described in the INDICATIONS AND USAGE section:

Aerobic Gram-Positive Microorganisms

Staphylococcus aureus (methicillin-susceptible strains)

Streptococcus pneumoniae (penicillin-susceptible strains)

Streptococcus pyogenes

Aerobic Gram-Negative Microorganisms

Citrobacter (diversus) koseri

Enterobacter aerogenes

Escherichia coli

Haemophilus influenzae

Klebsiella pneumoniae

Neisseria gonorrhoeae

Proteus mirabilis

Pseudomonas aeruginosa

As with other drugs in this class, some strains of Pseudomonas aeruginosa may develop resistance fairly rapidly during treatment with ofloxacin.

Other Microorganisms

Chlamydia trachomatis

The following in vitro data are available, but their clinical significance is unknown.

Ofloxacin exhibits in vitro minimum inhibitory concentrations (MIC values) of 2 mcg/mL or less against most (≥ 90%) strains of the following microorganisms; however, the safety and effectiveness of ofloxacin in treating clinical infections due to these microorganisms have not been established in adequate and well-controlled trials.

Aerobic Gram-Positive Microorganisms

Staphylococcus epidermidis (methicillin-susceptible strains)

Staphylococcus saprophyticus

Streptococcus pneumoniae (penicillin-resistant strains)

Aerobic Gram-Negative Microorganisms

Acinetobacter calcoaceticus

Bordetella pertussis

Citrobacter freundii

Enterobacter cloacae

Haemophilus ducreyi

Klebsiella oxytoca

Moraxella catarrhalis

Morganella morganii

Proteus vulgaris

Providencia rettgeri

Providencia stuartii

Serratia marcescens

Anaerobic Microorganisms

Clostridium perfringes

Other Microorganisms

Chlamydia pneumoniae

Gardnerella vaginalis

Legionella pneumophila

Mycoplasma hominis

Mycoplasma pneumoniae

Ureaplasma urealyticum

Ofloxacin is not active against Treponema pallidum (see WARNINGS).

Many strains of other streptococcal species, Enterococcus species, and anaerobes are resistant to ofloxacin.

Susceptibility Tests

Dilution Techniques

Quantitative methods are used to determine antimicrobial minimum inhibitory concentrations (MIC values). These MIC values provide estimates of the susceptibility of bacteria to antimicrobial compounds. The MIC values should be determined using a standardized procedure. Standardized procedures are based on a dilution method^1,3 (broth or agar) or equivalent with standardized inoculum concentrations and standardized concentrations of ofloxacin powder. The MIC values should be interpreted according to the following criteria:

For testing Enterobacteriaceae, methicillin-susceptible Staphylococcus aureus, and Pseudomonas aeruginosa:

MIC (mcg/mL) | Interpretation
≤ 2 | Susceptible (S)
4 | Intermediate (I)
≥ 8 | Resistant (R)

For testing Haemophilus influenzae:a

MIC (mcg/mL) | Interpretation
≤ 2 | Susceptible (S)

aThis interpretive standard is applicable only to broth microdilution susceptibility tests with Haemophilus influenzae using Haemophilus Test Medium.^1,3

The current absence of data on resistant strains precludes defining any results other than “Susceptible.” Strains yielding MIC results suggestive of a “nonsusceptible” category should be submitted to a reference laboratory for further testing.
For testing Neisseria gonorrhoeae:b

MIC (mcg/mL) | Interpretation
< 0.25 | Susceptible (S)
0.5 to 1 | Intermediate (I)
> 2 | Resistant (R)

bThese interpretive standards are applicable only to agar dilution tests using GC agar base and 1% defined growth supplement incubated in 5% CO2.
For testing Streptococcus pneumoniae and Streptococcus pyogenes:c

MIC (mcg/mL) | Interpretation
≤ 2 | Susceptible (S)
4 | Intermediate (I)
≥ 8 | Resistant (R)

c These interpretive standards are applicable only to broth microdilution susceptibility tests using cation-adjusted Mueller-Hinton broth with 2 to 5% lysed horse blood.

A report of “Susceptible” indicates that the pathogen is likely to be inhibited if the antimicrobial compound in the blood reaches the concentration usually achievable. A report of “Intermediate” indicates that the result should be considered equivocal, and, if the microorganism is not fully susceptible to alternative, clinically feasible drugs, the test should be repeated. This category implies possible clinical applicability in body sites where the drug is physiologically concentrated or in situations where a high dosage of drug can be used. This category also provides a buffer zone which prevents small uncontrolled technical factors from causing major discrepancies in interpretation. A report of “Resistant” indicates that the pathogen is not likely to be inhibited if the antimicrobial compound in the blood reaches the concentration usually achievable; other therapy should be selected.

Standardized susceptibility test procedures require the use of laboratory control microorganisms to control the technical aspects of the laboratory procedures. Standard ofloxacin powder should provide the following MIC values:

Microorganism |  | MIC Range (mcg/mL)
Escherichia coli | ATCC 25922 | 0.015 to 0.12
Haemophilus influenzae | ATCC 49247d | 0.016 to 0.06
Neisseria gonorrhoeae | ATCC 49226e | 0.004 to 0.016
Pseudomonas aeruginosa | ATCC 27853 | 1 to 8
Staphylococcus aureus | ATCC 29213 | 0.12 to 1
Streptococcus pneumoniae | ATCC 49619f | 1 to 4

dThis quality control range is applicable only to H. influenzae ATCC 49247 tested by a microdilution procedure using Haemophilus Test Medium (HTM).^1,3

e This quality control range is applicable only to N. gonorrhoeae ATCC 49226 tested by an agar dilution procedure using GC agar base with 1% defined growth supplement incubated in 5% CO2.

f This quality control range is applicable only to S. pneumoniae ATCC 49619 tested by a microdilution procedure using cation-adjusted Mueller-Hinton broth with 2 to 5% lysed horse blood.

Diffusion Techniques

Quantitative methods that require measurement of zone diameters also provide reproducible estimates of the susceptibility of bacteria to antimicrobial compounds. One such standardized procedure^2 requires the use of standardized inoculum concentrations. This procedure uses paper disks impregnated with 5 mcg ofloxacin to test the susceptibility of microorganisms to ofloxacin.

Reports from the laboratory providing results of the standard single-disk susceptibility test with a 5 mcg ofloxacin disk should be interpreted according to the following criteria:

For testing Enterobacteriaceae, methicillin-susceptible Staphylococcus aureus, and Pseudomonas aeruginosa:

Zone Diameter (mm) | Interpretation
≥ 16 | Susceptible (S)
13 to 15 | Intermediate (I)
≤ 12 | Resistant (R)

For testing Haemophilus influenzae:g

Zone Diameter (mm) | Interpretation
≥ 16 | Susceptible (S)

g This zone diameter standard is applicable only to disk diffusion tests with Haemophilus influenzae using Haemophilus Test Medium (HTM)^2 incubated in 5% CO2.

The current absence of data on resistant strains precludes defining any results other than “Susceptible.” Strains yielding zone diameter results suggestive of a “nonsusceptible” category should be submitted to a reference laboratory for further testing.

For testing Neisseria gonorrhoeae: h

Zone Diameter (mm) | Interpretation
≥ 31 | Susceptible (S)
25 to 30 | Intermediate (I)
≤ 24 | Resistant (R)

h These zone diameter standards are applicable only to disk diffusion tests using GC agar base and 1% defined growth supplement incubated in 5% CO2.

For testing Streptococcus pneumoniaeand Streptococcus pyogenes: i

Zone Diameter (mm) | Interpretation
≥ 16 | Susceptible (S)
13 to 15 | Intermediate (I)
≤ 12 | Resistant (R)

iThese zone diameter standards are applicable only to disk diffusion tests performed using Mueller-Hinton agar supplemented with 5% defibrinated sheep blood and incubated in 5% CO2.

Interpretation should be as stated above for results using dilution techniques. Interpretation involves correlation of the diameter obtained in the disk test with the MIC for ofloxacin.

As with standardized dilution techniques, diffusion methods require the use of laboratory control microorganisms that are used to control the technical aspects of the laboratory procedures. For the diffusion technique, the 5 mcg ofloxacin disk should provide the following zone diameters in these laboratory quality control strains:

Microorganism |  | Zone Diameter (mm)
Escherichia coli | ATCC 25922 | 29 to 33
Haemophilus influenzae | ATCC 49247j | 31 to 40
Neisseria gonorrhoeae | ATCC 49226k | 43 to 51
Pseudomonas aeruginosa | ATCC 27853 | 17 to 21
Staphylococcus aureus | ATCC 25923 | 24 to 28
Streptococcus pneumoniae | ATCC 49619l | 16 to 21

jThis quality control range is applicable only to H. influenzae ATCC 49247 tested by a disk diffusion procedure using Haemophilus Test Medium (HTM)^2 incubated in 5% CO2.

k This quality control range is applicable only to N. gonorrhoeae ATCC 49226 tested by a disk diffusion procedure using GC agar base with 1% defined growth supplement incubated in 5% CO2.

l This quality control range is applicable only to S. pneumoniae ATCC 49619 tested by a disk diffusion procedure using Mueller-Hinton agar supplemented with 5% defibrinated sheep blood and incubated in 5% CO2.

INDICATIONS AND USAGE

To reduce the development of drug-resistant bacteria and maintain the effectiveness of ofloxacin tablets, USP and other antibacterial drugs, ofloxacin tablets, USP should be used only to treat or prevent infections that are proven or strongly suspected to be caused by susceptible bacteria. When culture and susceptibility information are available, they should be considered in selecting or modifying antibacterial therapy. In the absence of such data, local epidemiology and susceptibility patterns may contribute to the empiric selection of therapy.
Ofloxacin tablets, USP are indicated for the treatment of adults with mild to moderate infections (unless otherwise indicated) caused by susceptible strains of the designated microorganisms in the infections listed below. Please see DOSAGE AND ADMINISTRATION for specific recommendations.
Acute Bacterial Exacerbations of Chronic Bronchitis (ABECB) due to Haemophilus influenzae or Streptococcus pneumoniae.

Because fluoroquinolones, including ofloxacin, have been associated with serious adverse reactions (see Warnings), -and for some patients ABECB is self-limiting, reserve ofloxacin for treatment of ABECB in patients who have no alternative treatment options.
Community-Acquired Pneumonia due to Haemophilus influenzae or Streptococcus pneumoniae.

Uncomplicated Skin and Skin Structure Infections due to methicillin-susceptible Staphylococcus aureus, Streptococcus pyogenes, or Proteus mirabilis.
Acute, Uncomplicated Urethral and Cervical Gonorrhea due to Neisseria gonorrhoeae (see WARNINGS).
Nongonococcal Urethritis and Cervicitis due to Chlamydia trachomatis (see WARNINGS).
Mixed Infections of the Urethra and Cervix due to Chlamydia trachomatis and Neisseria gonorrhoeae (see WARNINGS).
Acute Pelvic Inflammatory Disease (including severe infection) due to Chlamydia trachomatis and/or Neisseria gonorrhoeae (see WARNINGS).
NOTE: If anaerobic microorganisms are suspected of contributing to the infection, appropriate therapy for anaerobic pathogens should be administered.
Uncomplicated Cystitis due to Citrobacter diversus, Enterobacter aerogenes, Escherichia coli, Klebsiella pneumoniae, Proteus mirabilis, or Pseudomonas aeruginosa.
Because fluoroquinolones, including ofloxacin, have been associated with serious adverse reactions (see WARNINGS), and for some patients uncomplicated cystitis is self-limiting, reserve ofloxacin for treatment of uncomplicated cystitis in patients who have no alternative treatment options.
Complicated Urinary Tract Infections due to Escherichia coli, Klebsiella pneumoniae, Proteus mirabilis, Citrobacter diversus,* or Pseudomonas aeruginosa.*

Prostatitis due to Escherichia coli.
* = Although treatment of infections due to this organism in this organ system demonstrated a clinically significant outcome, efficacy was studied in fewer than 10 patients.

Appropriate culture and susceptibility tests should be performed before treatment in order to isolate and identify organisms causing the infection and to determine their susceptibility to ofloxacin, USP. Therapy with ofloxacin, USP may be initiated before results of these tests are known; once results become available, appropriate therapy should be continued.
As with other drugs in this class, some strains of Pseudomonas aeruginosa may develop resistance fairly rapidly during treatment with ofloxacin, USP. Culture and susceptibility testing performed periodically during therapy will provide information not only on the therapeutic effect of the antimicrobial agent but also on the possible emergence of bacterial resistance.

CONTRAINDICATIONS

Ofloxacin tablets are contraindicated in persons with a history of hypersensitivity associated with the use of ofloxacin or any member of the quinolone group of antimicrobial agents.

WARNINGS

Disabling and Potentially Irreversible Serious Adverse Reactions Including Tendinitis and Tendon Rupture, Peripheral Neuropathy, and Central Nervous System Effects
Fluoroquinolones, including ofloxacin, have been associated with disabling and potentially irreversible serious adverse reactions from different body systems that can occur together in the same patient. Commonly seen adverse reactions include tendinitis, tendon rupture, arthralgia, myalgia, peripheral neuropathy, and central nervous system effects (hallucinations, anxiety, depression, insomnia, severe headaches, and confusion). These reactions can occur within hours to weeks after starting ofloxacin. Patients of any age or without pre-existing risk factors have experienced these adverse reactions (see Warnings)
Discontinue ofloxacin immediately at the first signs or symptoms of any serious adverse reaction. In addition, avoid the use of fluoroquinolones, including ofloxacin, in patients who have experienced any of these serious adverse reactions associated with fluoroquinolones.
Tendinitis and Tendon Rupture
Fluoroquinolones, including ofloxacin, have been associated with an increased risk of tendinitis and tendon rupture in all ages. This adverse reaction most frequently involves the Achilles tendon, and rupture of the Achilles tendon and has been reported with the rotator cuff (the shoulder), the hand, the biceps, the thumb, and other tendons. Tendinitis or tendon rupture can occur within hours or days of starting ofloxacin, or as long as several months after completion of fluoroquinolone therapy. Tendinitis and tendon rupture can occur bilaterally.
The risk of developing fluoroquinolone-associated tendinitis and tendon rupture is increased in patients over 60 years of age, in those taking corticosteroid drugs, and in patients with kidney, heart or lung transplants. Other factors that may independently increase the risk of tendon rupture include strenuous physical activity, renal failure, and previous tendon disorders such as rheumatoid arthritis. Tendinitis and tendon rupture have been reported in patients taking fluoroquinolones who do not have the above risk factors. Discontinue ofloxacin immediately if the patient experiences pain, swelling, inflammation or rupture of a tendon. Avoid fluoroquinolones, including ofloxacin, in patients who have a history of tendon disorders or have experienced tendinitis or tendon rupture (see Adverse Reactions). Patients should be advised to rest at the first sign of tendinitis or tendon rupture, and to contact their healthcare provider regarding changing to a non-quinolone antimicrobial drug.
Peripheral Neuropathy
Fluoroquinolones, including ofloxacin, have been associated with an increased risk of peripheral neuropathy. Cases of sensory or sensorimotor axonal polyneuropathy affecting small and/or large axons resulting in paresthesias, hypoesthesias, dysesthesias and weakness have been reported in patients receiving fluoroquinolones, including ofloxacin. Symptoms may occur soon after initiation of norfloxacin and may be irreversible in some patients (see WARNINGS).
Discontinue ofloxacin immediately if the patient experiences symptoms of peripheral neuropathy including pain, burning, tingling, numbness, and/or weakness, or other alterations in sensations including light touch, pain, temperature, position sense and vibratory sensation, and/or motor strength in order to minimize the development of an irreversible condition. Avoid fluoroquinolones, including ofloxacin, in patients who have previously experienced peripheral neuropathy (see Adverse Reactions).
Central Nervous System Effects
Psychiatric Adverse Reactions: Fluoroquinolones, including ofloxacin, have been associated with an increased risk of psychiatric adverse reactions toxic psychoses or hallucinations; agitation; delirium, confusion, disorientation, or disturbances in attention; nervousness or restlessness, memory impairment. If these reactions occur in patients receiving ofloxacin, the drug should be discontinued and appropriate measures instituted.
Central Nervous System Adverse Reactions: Fluoroquinolones have been associated with an increased risk of seizures (convulsions), increased intracranial pressure (pseudotumor cerebri), lightheadedness, or tremors.The effects of ofloxacin on brain function or on the electrical activity of the brain have not been tested. Therefore, until more information becomes available, ofloxacin, like all other quinolones, should be used with caution in patients with known or suspected CNS disorders, such as severe cerebral arteriosclerosis, epilepsy, and other factors which predispose to seizures (see ADVERSE REACTIONS).
Exacerbation of Myasthenia Gravis Fluoroquinolones, including ofloxacin, have neuromuscular blocking activity and may exacerbate muscle weakness in persons with myasthenia gravis. Postmarketing serious adverse events, including deaths and requirement for ventilatory support, have been associated with fluoroquinolone use in persons with myasthenia gravis. Avoid ofloxacin

in patients with known history of myasthenia gravis (see PRECAUTIONS, Information for Patients and ADVERSE REACTIONS, Postmarketing Adverse Events).
THE SAFETY AND EFFICACY OF OFLOXACIN IN PEDIATRIC PATIENTS AND ADOLESCENTS (UNDER THE AGE OF 18 YEARS), PREGNANT WOMEN, AND LACTATING WOMEN HAVE NOT BEEN ESTABLISHED (see PRECAUTIONS, Pediatric Use, Pregnancy, and Nursing Mothers Subsections).
In the immature rat, the oral administration of ofloxacin at 5 to 16 times the recommended maximum human dose based on mg/kg or 1 to 3 times based on mg/m^2 increased the incidence and severity of osteochondrosis. The lesions did not regress after 13 weeks of drug withdrawal. Other quinolones also produce similar erosions in the weight-bearing joints and other signs of arthropathy in immature animals of various species (see ANIMAL PHARMACOLOGY).
Hypersensitivity Reactions
Serious and occasionally fatal hypersensitivity and/or anaphylactic reactions have been reported in patients receiving therapy with quinolones, including ofloxacin. These reactions often occur following the first dose. Some reactions have been accompanied by cardiovascular collapse, hypotension/shock, seizure, loss of consciousness, tingling, angioedema (including tongue, laryngeal, throat, or facial edema/swelling), airway obstruction (including bronchospasm, shortness of breath, and acute respiratory distress), dyspnea, urticaria, itching, and other serious skin reactions. This drug should be discontinued immediately at the first appearance of a skin rash or any other sign of hypersensitivity. Serious acute hypersensitivity reactions may require treatment with epinephrine and other resuscitative measures, including oxygen, intravenous fluids, antihistamines, corticosteroids, pressor amines, and airway management, as clinically indicated (see PRECAUTIONS and ADVERSE REACTIONS).
Other serious and sometimes fatal events, some due to hypersensitivity, and some due to uncertain etiology, have been reported rarely in patients receiving therapy with quinolones, including ofloxacin. These events may be severe and generally occur following the administration of multiple doses. Clinical manifestations may include one or more of the following:
• fever, rash, or severe dermatologic reactions (e.g., toxic epidermal necrolysis, Stevens-Johnson syndrome);
• vasculitis; arthralgia; myalgia; serum sickness;
• allergic pneumonitis;
• interstitial nephritis; acute renal insufficiency or failure;
• hepatitis; jaundice; acute hepatic necrosis or failure;
• anemia, including hemolytic and aplastic; thrombocytopenia, including thrombotic thrombocytopenic purpura; leukopenia; agranulocytosis; pancytopenia; and/or other hematologic abnormalities.
The drug should be discontinued immediately at the first appearance of skin rash, jaundice, or any other sign of hypersensitivity and supportive measures instituted (see PRECAUTIONS, Information for Patients and ADVERSE REACTIONS).
Clostridium difficile associated diarrhea (CDAD) has been reported with use of nearly all antibacterial agents, including ofloxacin tablets, and may range in severity from mild diarrhea to fatal colitis. Treatment with antibacterial agents alters the normal flora of the colon leading to overgrowth of C. difficile.
C. difficile produces toxins A and B which contribute to the development of CDAD. Hypertoxin producing strains of C. difficile cause increased morbidity and mortality, as these infections can be refractory to antimicrobial therapy and may require colectomy. CDAD must be considered in all patients who present with diarrhea following antibiotic use. Careful medical history is necessary since CDAD has been reported to occur over two months after the administration of antibacterial agents.
If CDAD is suspected or confirmed, ongoing antibiotic use not directed against C. difficile may need to be discontinued. Appropriate fluid and electrolyte management, protein supplementation, antibiotic treatment of C. difficile, and surgical evaluation should be instituted as clinically indicated (see ADVERSE REACTIONS).
Risk of Aortic Aneurysm and Dissection
Epidemiologic studies report an increased rate of aortic aneurysm and dissection within two months following use of fluoroquinolones, particularly in elderly patients. The cause for the increased risk has not been identified. In patients with a known aortic aneurysm or patients who are at greater risk for aortic aneurysms, reserve ofloxacin for use only when there are no alternative antibacterial treatments available.
Ofloxacin has not been shown to be effective in the treatment of syphilis.
Fluoroquinolones have been associated with disturbances of blood glucose, including symptomatic hyperglycemia and hypoglycemia, usually in diabetic patients receiving concomitant treatment with an oral hypoglycemic agent (e.g., glyburide) or with insulin. In these patients, careful monitoring of blood glucose is recommended. Severe cases of hypoglycemia resulting in coma or death have been reported. If a hypoglycemic reaction occurs in a patient being treated with ofloxacin, discontinue ofloxacin and initiate appropriate therapy immediately.
Antimicrobial agents used in high doses for short periods of time to treat gonorrhea may mask or delay the symptoms of incubating syphilis. All patients with gonorrhea should have a serologic test for syphilis at the time of diagnosis. Patients treated with ofloxacin for gonorrhea should have a follow-up serologic test for syphilis after three months and, if positive, treatment with an appropriate antimicrobial should be instituted.

PRECAUTIONS

General

Prescribing ofloxacin tablets in the absence of a proven or strongly suspected bacterial infection or a prophylactic indication is unlikely to provide benefit to the patient and increases the risk of the development of drug-resistant bacteria.
Adequate hydration of patients receiving ofloxacin should be maintained to prevent the formation of a highly concentrated urine.
Administer ofloxacin with caution in the presence of renal or hepatic insufficiency/impairment. In patients with known or suspected renal or hepatic insufficiency/impairment, careful clinical observation and appropriate laboratory studies should be performed prior to and during therapy since elimination of ofloxacin may be reduced. In patients with impaired renal function (creatinine clearance ≤ 50 mg/mL), alteration of the dosage regimen is necessary(see CLINICAL PHARMACOLOGY and DOSAGE AND ADMINISTRATION).
Moderate to severe photosensitivity/phototoxicity reactions, the latter of which may manifest as exaggerated sunburn reactions (e.g., burning, erythema, exudation, vesicles, blistering, edema) involving areas exposed to light (typically the face, “V” area of the neck, extensor surfaces of the forearms, dorsa of the hands), can be associated with the use of quinolones after sun or UV light exposure. Therefore, excessive exposure to these sources of light should be avoided. Drug therapy should be discontinued if photosensitivity/phototoxicity occurs (See ADVERSE REACTIONS, Postmarketing Adverse Events).
As with other quinolones, ofloxacin should be used with caution in any patient with a known or suspected CNS disorder that may predispose to seizures or lower the seizure threshold (e.g., severe cerebral arteriosclerosis, epilepsy) or in the presence of other risk factors that may predispose to seizures or lower the seizure threshold (e.g., certain drug therapy, renal dysfunction) (see WARNINGS and Drug Interactions).
A possible interaction between oral hypoglycemic drugs (e.g., glyburide/glibenclamide) or with insulin and fluoroquinolone antimicrobial agents have been reported resulting in a potentiation of the hypoglycemic action of these drugs, sometimes resulting in coma or death. The mechanism for this interaction is not known. If a hypoglycemic reaction occurs in a patient being treated with ofloxacin, discontinue ofloxacin immediately and consult a physician (see Drug Interactions and ADVERSE REACTIONS).
As with any potent drug, periodic assessment of organ system functions, including renal, hepatic, and hematopoietic, is advisable during prolonged therapy (see WARNINGS and ADVERSE REACTIONS).
Torsade de Pointes

Some quinolones, including ofloxacin, have been associated with prolongation of the QT interval on the electrocardiogram and infrequent cases of arrhythmia. Rare cases of torsade de pointes have been spontaneously reported during postmarketing surveillance in patients receiving quinolones, including ofloxacin. Ofloxacin should be avoided in patients with known prolongation of the QT interval, patients with uncorrected hypokalemia, and patients receiving Class IA (quinidine, procainamide), or Class III (amiodarone, sotalol) antiarrhythmic agents.

Information for Patients

Advise the patient to read the FDA-approved patient labeling (Medication Guide)
Serious Adverse Reactions
Advise patients to stop taking ofloxacin if they experience an adverse reaction and to call their healthcare provider for advice on completing the full course of treatment with another antibacterial drug.
Inform patients of the following serious adverse reactions that have been associated with NOROXIN or other fluoroquinolone use:
• Disabling and potentially irreversible serious adverse reactions that may occur together: Inform patients that disabling and potentially irreversible serious adverse reactions, including tendinitis and tendon rupture, peripheral neuropathies, and central nervous system effects, have been associated with use of ofloxacin and may occur together in the same patient. Inform patients to stop taking ofloxacin immediately if they experience an adverse reaction and to call their healthcare provider.
• Tendon Disorders: instruct patients to contact their healthcare provider if they experience pain, swelling, or inflammation of a tendon, or weakness or inability to use one of their joints; rest and refrain from exercise; and discontinue ofloxacin treatment. The risk of severe tendon disorders with fluoroquinolones is higher in older patients usually over 60 years of age, in patients taking corticosteroid drugs, and in patients with kidney, heart or lung transplants.
• Peripheral Neuropathies: Inform patients that peripheral neuropathies have been associated with the use of ofloxacin, that symptoms may occur soon after initiation of therapy and may be irreversible. If symptoms of peripheral neuropathy including pain, burning, tingling, numbness, and/or weakness develop, patients should immediately discontinue ofloxacin and contact their physicians.
• Central nervous system effects (for example, convulsions, dizziness, lightheadedness, increased intracranial pressure): Inform patients that convulsions have been reported in patients receiving fluoroquinolones, including ofloxacin. Instruct patients to notify their physician before taking this drug if they have a history of convulsions. Inform patients that they should know how they react to ofloxacin before they operate an automobile or machinery or engage in other activities requiring mental alertness and coordination. Instruct patients to notify their physician if persistent headache with or without blurred vision occurs.
• Myasthenia gravis: inform patients that fluoroquinolones like ofloxacin may cause worsening of myasthenia gravis symptoms, including muscle weakness and breathing problems. Patients should call their healthcare provider right away if you have any worsening muscle weakness or breathing problems.
• Hypersensitivity Reactions: Inform patients that ofloxacin can cause hypersensitivity reactions, even following a single dose, and to discontinue the drug at the first sign of a skin rash, hives or other skin reactions, a rapid heartbeat, difficulty in swallowing or breathing, any swelling suggesting angioedema (for example, swelling of the lips, tongue, face, tightness of the throat, hoarseness), or other symptoms of an allergic reaction.
• Hepatotoxicity: Inform patients that severe hepatotoxicity (including acute hepatitis and fatal events) has been reported in patients taking ofloxacin. Instruct patients to inform their physician if they experience any signs or symptoms of liver injury including: loss of appetite, nausea, vomiting, fever, weakness, tiredness, right upper quadrant tenderness, itching, yellowing of the skin and eyes, light colored bowel movements or dark colored urine.
• Diarrhea: Diarrhea is a common problem caused by antibiotics which usually ends when the antibiotic is discontinued. Sometimes after starting treatment with antibiotics, patients can develop watery and bloody stools (with or without stomach cramps and fever) even as late as two or more months after having taken the last dose of the antibiotic. If this occurs, instruct patients to contact their physician as soon as possible.
• Photosensitivity/Phototoxicity: Inform patients that photosensitivity/phototoxicity has been reported in patients receiving fluoroquinolones. Patients should minimize or avoid exposure to natural or artificial sunlight (tanning beds or UVA/B treatment) while taking quinolones. If patients need to be outdoors while using quinolones, they should wear loose-fitting clothes that protect skin from sun exposure and discuss other sun protection measures with their physician. If a sunburn-like reaction or skin eruption occurs, patients should contact their physician.
Other Information
Patients should be advised:
• to drink fluids liberally.
• that mineral supplements, vitamins with iron or minerals, calcium-, aluminum- or magnesium-based antacids, sucralfate or didanosine chewable/buffered tablets or the pediatric powder for oral solution should not be taken within the two-hour period before or within the two-hour period after taking ofloxacin (see Drug Interactions)
• that ofloxacin can be taken without regard to meals
• Patients should be counseled that antibacterial drugs including ofloxacin tablets should only be used to treat bacterial infections. They do not treat viral infections (e.g., the common cold). When ofloxacin tablets are prescribed to treat a bacterial infection, patients should be told that although it is common to feel better early in the course of therapy, the medication should be taken exactly as directed. Skipping doses or not completing the full course of therapy may (1) decrease the effectiveness of the immediate treatment and (2) increase the likelihood that bacteria will develop resistance and will not be treatable by ofloxacin tablets or other antibacterial drugs in the future.
• that if they are diabetic and are being treated with insulin or an oral hypoglycemic drug, to discontinue ofloxacin immediately if a hypoglycemic reaction occurs and consult a physician (see PRECAUTIONS, General and Drug Interactions);
• that convulsions have been reported in patients taking quinolones, including ofloxacin, and to notify their physician before taking this drug if there is a history of this condition;
• to inform their physician of any personal or family history of QTC prolongation or proarrhythmic conditions such as hypokalemia, bradycardia, or recent myocardial ischemia; if they are taking any class IA (quinidine, procainamide), or class III (amiodarone, sotalol) antiarrhythmic agents. Patients should notify their physicians if they have any symptoms of prolongation of the QTC interval including prolonged heart palpitations or a loss of consciousness.
• Aortic aneurysm and dissection: Inform patients to seek emergency medical care if they experience sudden chest, stomach, or back pain.

Drug Interactions

Antacids, Sucralfate, Metal Cations, Multivitamins
Quinolones form chelates with alkaline earth and transition metal cations. Administration of quinolones with antacids containing calcium, magnesium, or aluminum, with sucralfate, with divalent or trivalent cations such as iron, or with multivitamins containing zinc or with didanosine, chewable/buffered tablets or the pediatric powder for oral solution may substantially interfere with the absorption of quinolones resulting in systemic levels considerably lower than desired. These agents should not be taken within the two-hour period before or within the two-hour period after ofloxacin administration (see DOSAGE AND ADMINISTRATION).

Caffeine
Interactions between ofloxacin and caffeine have not been detected.

Cimetidine
Cimetidine has demonstrated interference with the elimination of some quinolones. This interference has resulted in significant increases in half-life and AUC of some quinolones. The potential for interaction between ofloxacin and cimetidine has not been studied.

Cyclosporine
Elevated serum levels of cyclosporine have been reported with concomitant use of cyclosporine with some other quinolones. The potential for interaction between ofloxacin and cyclosporine has not been studied.

Drugs Metabolized by Cytochrome P450 Enzymes
Most quinolone antimicrobial drugs inhibit cytochrome P450 enzyme activity. This may result in a prolonged half-life for some drugs that are also metabolized by this system (e.g., cyclosporine, theophylline/methylxanthines, warfarin) when coadministered with quinolones. The extent of this inhibition varies among different quinolones (see other Drug Interactions).

Non Steroidal Anti-Inflammatory Drugs
The concomitant administration of a non-steroidal anti-inflammatory drug with a quinolone, including ofloxacin, may increase the risk of CNS stimulation and convulsive seizures (see WARNINGS and PRECAUTIONS , General).

Probenecid
The concomitant use of probenecid with certain other quinolones has been reported to affect renal tubular secretion. The effect of probenecid on the elimination of ofloxacin has not been studied.

Theophylline
Steady-state theophylline levels may increase when ofloxacin and theophylline are administered concurrently. As with other quinolones, concomitant administration of ofloxacin may prolong the half-life of theophylline, elevate serum theophylline levels, and increase the risk of theophylline-related adverse reactions. Theophylline levels should be closely monitored and theophylline dosage adjustments made, if appropriate, when ofloxacin is coadministered. Adverse reactions (including seizures) may occur with or without an elevation in the serum theophylline level (see WARNINGS and PRECAUTIONS , General).

Warfarin
Some quinolones have been reported to enhance the effects of the oral anticoagulant warfarin or its derivatives. Therefore, if a quinolone antimicrobial is administered concomitantly with warfarin or its derivatives, the prothrombin time or other suitable coagulation test should be closely monitored.

Antidiabetic Agents (e.g., Insulin, Glyburide/Glibenclamide)
Since disturbances of blood glucose, including hyperglycemia and hypoglycemia, have been reported in patients treated concurrently with quinolones and an antidiabetic agent, careful monitoring of blood glucose is recommended when these agents are used concomitantly (see PRECAUTIONS , General and Information for Patients).

Interaction With Laboratory or Diagnostic Testing

Some quinolones, including ofloxacin, may produce false-positive urine screening results for opiates using commercially available immunoassay kits. Confirmation of positive opiate screens by more specific methods may be necessary.

Carcinogenesis, Mutagenesis, Impairment of Fertility

Long-term studies to determine the carcinogenic potential of ofloxacin have not been conducted.
Ofloxacin was not mutagenic in the Ames bacterial test, in vitro and in vivo cytogenetic assay, sister chromatid exchange (Chinese Hamster and Human Cell Lines), unscheduled DNA Repair (UDS) using human fibroblasts, dominant lethal assays, or mouse micronucleus assay. Ofloxacin was positive in the UDS test using rat hepatocytes and Mouse Lymphoma Assay.

Pregnancy

Teratogenic Effects

Pregnancy Category C
Ofloxacin has not been shown to have any teratogenic effects at oral doses as high as 810 mg/kg/day (11 times the recommended maximum human dose based on mg/m^2 or 50 times based on mg/kg) and 160 mg/kg/day (4 times the recommended maximum human dose based on mg/m^2 or 10 times based on mg/kg) when administered to pregnant rats and rabbits, respectively. Additional studies in rats with oral doses up to 360 mg/kg/day (5 times the recommended maximum human dose based on mg/m^2 or 23 times based on mg/kg) demonstrated no adverse effect on late fetal development, labor, delivery, lactation, neonatal viability, or growth of the newborn. Doses equivalent to 50 and 10 times the recommended maximum human dose of ofloxacin (based on mg/kg) were fetotoxic (i.e., decreased fetal body weight and increased fetal mortality) in rats and rabbits, respectively. Minor skeletal variations were reported in rats receiving doses of 810 mg/kg/day, which is more than 10 times higher than the recommended maximum human dose based on mg/m^2.
There are, however, no adequate and well-controlled studies in pregnant women. Ofloxacin should be used during pregnancy only if the potential benefit justifies the potential risk to the fetus (see WARNINGS).

Nursing Mothers

In lactating females, a single oral 200 mg dose of ofloxacin resulted in concentrations of ofloxacin in milk that were similar to those found in plasma. Because of the potential for serious adverse reactions from ofloxacin in nursing infants, a decision should be made whether to discontinue nursing or to discontinue the drug, taking into account the importance of the drug to the mother (see WARNINGS and ADVERSE REACTIONS).

Pediatric Use

Safety and effectiveness in pediatric patients and adolescents below the age of 18 years have not been established. Ofloxacin causes arthropathy (arthrosis) and osteochondrosis in juvenile animals of several species (see WARNINGS).

Geriatric Use

Geriatric patients are at increased risk for developing severe tendon disorders including tendon rupture when being treated with a fluoroquinolone such as ofloxacin. This risk is further increased in patients receiving concomitant corticosteroid therapy. Tendinitis or tendon rupture can involve the Achilles, hand, shoulder, or other tendon sites and can occur during or after completion of therapy; cases occurring up to several months after fluoroquinolone treatment have been reported. Caution should be used when prescribing ofloxacin to elderly patients especially those on corticosteroids. Patients should be informed of this potential side effect and advised to discontinue ofloxacin and contact their healthcare provider if any symptoms of tendinitis or tendon rupture occur (See Boxed Warning; WARNINGS; and ADVERSE REACTIONS, Postmarketing Adverse Event Reports).
In phase 2/3 clinical trials with ofloxacin, 688 patients (14.2%) were ≥ 65 years of age. Of these, 436 patients (9%) were between the ages of 65 and 74 and 252 patients (5.2%) were 75 years or older. There was no apparent difference in the frequency or severity of adverse reactions in elderly adults compared with younger adults. The pharmacokinetic properties of ofloxacin in elderly subjects are similar to those in younger subjects. Drug absorption appears to be unaffected by age. Dosage adjustment is necessary for elderly patients with impaired renal function (creatinine clearance rate ≤ 50 mL/min) due to reduced clearance of ofloxacin. In comparative studies, the frequency and severity of most drug-related nervous system events in patients ≥65 years of age were comparable for ofloxacin and control drugs. The only differences identified were an increase in reports of insomnia (3.9% vs. 1.5%) and headache (4.7% vs. 1.8%) with ofloxacin. It is important to note that these geriatric safety data are extracted from 44 comparative studies where the adverse reaction information from 20 different controls (other antibiotics or placebo) were pooled for comparison with ofloxacin. The clinical significance of such a comparison is not clear (see CLINICAL PHARMACOLOGY and DOSAGE AND ADMINISTRATION).
Elderly patients may be more sensitive to drug-associated effects on the QT interval. Therefore, precaution should be taken when using ofloxacin with concomitant drugs that can result in prolongation of the QT interval (e.g. Class IA or Class III antiarrhythmics) or in patients with risk factors for torsade de pointes (e.g. known QT prolongation, uncorrected hypokalemia) (see PRECAUTIONS, General, Torsade de Pointes).
Epidemiologic studies report an increased rate of aortic aneurysm and dissection within two months following use of fluoroquinolones, particularly in elderly patients [see Warnings].

ADVERSE REACTIONS

The following is a compilation of the data for ofloxacin based on clinical experience with both the oral and intravenous formulations. The incidence of drug-related adverse reactions in patients during Phase 2 and 3 clinical trials was 11%. Among patients receiving multiple-dose therapy, 4% discontinued ofloxacin due to adverse experiences.
In clinical trials, the following events were considered likely to be drug-related in patients receiving multiple doses of ofloxacin:
nausea 3%, insomnia 3%, headache 1%, dizziness 1%, diarrhea 1%, vomiting 1%, rash 1%, pruritus 1%, external genital pruritus in women 1%, vaginitis 1%, dysgeusia 1%.
In clinical trials, the most frequently reported adverse events, regardless of relationship to drug, were:
nausea 10%, headache 9%, insomnia 7%, external genital pruritus in women 6%, dizziness 5%, vaginitis 5%, diarrhea 4%, vomiting 4%.

In clinical trials, the following events, regardless of relationship to drug, occurred in 1 to 3% of patients:
abdominal pain and cramps, chest pain, decreased appetite, dry mouth, dysgeusia, fatigue, flatulence, gastrointestinal distress, nervousness, pharyngitis, pruritus, fever, rash, sleep disorders, somnolence, trunk pain, vaginal discharge, visual disturbances, and constipation.
Additional events, occurring in clinical trials at a rate of less than 1%, regardless of relationship to drug, were:

Body as a Whole: | asthenia, chills, malaise, extremity pain, pain, epistaxis
Cardiovascular System: | cardiac arrest, edema, hypertension, hypotension, palpitations, vasodilation
Gastrointestinal System: | dyspepsia
Genital/Reproductive System: | burning, irritation, pain and rash of the female genitalia; dysmenorrhea; menorrhagia; metrorrhagia
Musculoskeletal System: | arthralgia, myalgia
Nervous System: | seizures, anxiety, cognitive change, depression, dream abnormality, euphoria, hallucinations, paresthesia, syncope, vertigo, tremor, confusion
Nutritional/Metabolic: | thirst, weight loss
Respiratory System: | respiratory arrest, cough, rhinorrhea
Skin/Hypersensitivity: | angioedema, diaphoresis, urticaria, vasculitis
Special Senses: | decreased hearing acuity, tinnitus, photophobia
Urinary System: | dysuria, urinary frequency, urinary retention

The following laboratory abnormalities appeared in ≥ 1% of patients receiving multiple doses of ofloxacin. It is not known whether these abnormalities were caused by the drug or the underlying conditions being treated.

Hematopoietic: | anemia, leukopenia, leukocytosis, neutropenia, neutrophilia, increased band forms, lymphocytopenia, eosinophilia, lymphocytosis, thrombocytopenia, thrombocytosis, elevated ESR
Hepatic: | elevated: alkaline phosphatase, AST (SGOT), ALT (SGPT)
Serum Chemistry: | hyperglycemia, hypoglycemia, elevated creatinine, elevated BUN
Urinary: | glucosuria, proteinuria, alkalinuria, hyposthenuria, hematuria, pyuria

Postmarketing Adverse Events
Additional adverse events, regardless of relationship to drug, reported from worldwide marketing experience with quinolones, including ofloxacin:
Clinical

Cardiovascular System: | cerebral thrombosis, pulmonary edema, tachycardia, hypotension/shock, syncope, torsade de pointes.
Endocrine/Metabolic: | hyper- or hypoglycemia, especially in diabetic patients on insulin or oral hypoglycemic agents (see PRECAUTIONS, General and Drug Interactions).
Gastrointestinal System: | hepatic dysfunction including: hepatic necrosis, jaundice (cholestatic or hepatocellular), hepatitis; intestinal perforation; hepatic failure (including fatal cases); pseudomembranous colitis (the onset of pseudomembranous colitis symptoms may occur during or after antimicrobial treatment), GI hemorrhage; hiccough, painful oral mucosa, pyrosis (see WARNINGS).
Genital/Reproductive System: | vaginal candidiasis
Hematopoietic: | anemia, including hemolytic and aplastic; hemorrhage, pancytopenia, agranulocytosis, leukopenia, reversible bone marrow depression, thrombocytopenia, thrombotic thrombocytopenic purpura, petechiae, ecchymosis/bruising (see WARNINGS).
Musculoskeletal: | tendinitis/rupture; weakness; rhabdomyolysis (see WARNINGS).
Nervous System: | nightmares; suicidal thoughts or acts, disorientation, psychotic reactions, paranoia; phobia, agitation, restlessness, aggressiveness/hostility, manic reaction, emotional lability; peripheral neuropathy that may be irreversible, ataxia, incoordination; exacerbation of: myasthenia gravis and extrapyramidal disorders; dysphasia, lightheadedness (see WARNINGS and PRECAUTIONS).
Respiratory System: | dyspnea, bronchospasm, allergic pneumonitis, stridor (see WARNINGS).
Skin/Hypersensitivity: | anaphylactic (-toid) reactions/shock; purpura, serum sickness, erythema multiforme/Stevens-Johnson syndrome, erythema nodosum, exfoliative dermatitis, hyperpigmentation, toxic epidermal necrolysis, conjunctivitis, photosensitivity/phototoxicity reaction, vesiculobullous eruption (see WARNINGS and PRECAUTIONS).
Special Senses: | diplopia, nystagmus, blurred vision, disturbances of: taste, smell, hearing and equilibrium, usually reversible following discontinuation
Urinary System: | anuria, polyuria, renal calculi, renal failure, interstitial nephritis, hematuria (see WARNINGS and PRECAUTIONS).

Laboratory

Hematopoietic: | prolongation of prothrombin time
Serum Chemistry: | acidosis, elevation of: serum triglycerides, serum cholesterol, serum potassium, liver function tests including: GGTP, LDH, bilirubin
Urinary: | albuminuria, candiduria

In clinical trials using multiple-dose therapy, ophthalmologic abnormalities, including cataracts and multiple punctate lenticular opacities, have been noted in patients undergoing treatment with other quinolones. The relationship of the drugs to these events is not presently established.
CRYSTALLURIA and CYLINDRURIA HAVE BEEN REPORTED with other quinolones.

OVERDOSAGE

Information on overdosage with ofloxacin is limited. One incident of accidental overdosage has been reported. In this case, an adult female received 3 grams of ofloxacin intravenously over 45 minutes. A blood sample obtained 15 minutes after the completion of the infusion revealed an ofloxacin level of 39.3 mcg/mL. In 7 h, the level had fallen to 16.2 mcg/mL, and by 24 h to 2.7 mcg/mL. During the infusion, the patient developed drowsiness, nausea, dizziness, hot and cold flushes, subjective facial swelling and numbness, slurring of speech, and mild to moderate disorientation. All complaints except the dizziness subsided within 1 h after discontinuation of the infusion. The dizziness, most bothersome while standing, resolved in approximately 9 h. Laboratory testing reportedly revealed no clinically significant changes in routine parameters in this patient.

In the event of an acute overdose, the stomach should be emptied. The patient should be observed and appropriate hydration maintained. Ofloxacin is not efficiently removed by hemodialysis or peritoneal dialysis.

DOSAGE AND ADMINISTRATION

The usual dose of ofloxacin tablets is 200 mg to 400 mg orally every 12 h as described in the following dosing chart. These recommendations apply to patients with normal renal function (i.e., creatinine clearance > 50 mL/min). For patients with altered renal function (i.e., creatinine clearance < 50 mL/min), see the Patients With Impaired Renal Function subsection.

Infection† | Unit Dose | Frequency | Duration | Daily Dose
Acute Bacterial Exacerbation of Chronic Bronchitis | 400 mg | q12h | 10 days | 800 mg
Comm. Acquired Pneumonia | 400 mg | q12h | 10 days | 800 mg
Uncomplicated Skin and Skin Structure Infections | 400 mg | q12h | 10 days | 800 mg
Acute, Uncomplicated Urethral and Cervical Gonorrhea | 400 mg | single dose | 1 day | 400 mg
Nongonococcal Cervicitis/Urethritis due to C. trachomatis | 300 mg | q12h | 7 days | 600 mg
Mixed Infection of the Urethra and Cervix due to C. trachomatis and N. gonorrhoeae | 300 mg | q12h | 7 days | 600 mg
Acute Pelvic Inflammatory Disease | 400 mg | q12h | 10 to 14 days | 800 mg
Uncomplicated Cystitis due to E. coli or K. pneumoniae | 200 mg | q12h | 3 days | 400 mg
Uncomplicated Cystitis due to Other Approved Pathogens | 200 mg | q12h | 7 days | 400 mg
Complicated UTI’s | 200 mg | q12h | 10 days | 400 mg
Prostatitis due to E. coli | 300 mg | q12h | 6 weeks | 600 mg
† DUE TO THE DESIGNATED PATHOGENS (see INDICATIONS AND USAGE).

Antacids containing calcium, magnesium, or aluminum; sucralfate; divalent or trivalent cations such as iron; or multivitamins containing zinc; or didanosine, chewable/buffered tablets or the pediatric powder for oral solution should not be taken within the two-hour period before or within the two-hour period after taking ofloxacin (see PRECAUTIONS).
Patients With Impaired Renal Function
Dosage should be adjusted for patients with a creatinine clearance < 50 mL/min. After a normal initial dose, dosage should be adjusted as follows:

Creatinine Clearance | Maintenance Dose | Frequency
20 to 50 mL/min | the usual recommended unit dose | q24h
< 20 mL/min | ½ the usual recommended unit dose | q24h

When only the serum creatinine is known, the following formula may be used to estimate creatinine clearance.
Women: 0.85 x the value calculated for men.
The serum creatinine should represent a steady-state of renal function.

Patients With Cirrhosis:

The excretion of ofloxacin may be reduced in patients with severe liver function disorders (e.g., cirrhosis with or without ascites). A maximum dose of 400 mg of ofloxacin per day should therefore not be exceeded.

HOW SUPPLIED

Ofloxacin tablets USP, 200 mg are available as light yellow to yellow, oval, biconvex, film coated tablets, imprinted with “C213” in blue ink on one side and plain on the other side. They are available in bottles of 50, 100 and 500 tablets.

Bottles of 50 (NDC 72241-072-02)
Bottles of 100 (NDC 72241-072-05)
Bottles of 500 (NDC 72241-072-10)

Ofloxacin tablets USP, 300 mg are available as white to off white, oval, biconvex, film coated tablets, imprinted with “C212” in blue ink on one side and plain on the other side. They are available in bottles of 50, 100 and 500 tablets.

Bottles of 50 (NDC 72241-073-02)
Bottles of 100 (NDC 72241-073-05)
Bottles of 500 (NDC 72241-073-10)

Ofloxacin tablets USP, 400 mg are available as yellow to dark yellow, oval, biconvex, film coated tablets, imprinted with ‘C211’ in blue ink on one side and plain on other side. They are available in bottles of 50, 100 and 500 tablets.

Bottles of 50 (NDC 72241-074-02)
Bottles of 100 (NDC 72241-074-05)
Bottles of 500 (NDC 72241-074-10)

Store at 20° to 25°C (68° to 77°F) [See USP Controlled Room Temperature]. Dispense in a tight, light-resistant container as defined in the USP, with a child-resistant closure (as required)
KEEP THIS AND ALL MEDICATIONS OUT OF THE REACH OF CHILDREN.

ANIMAL PHARMACOLOGY

Ofloxacin, as well as other drugs of the quinolone class, has been shown to cause arthropathies (arthrosis) in immature dogs and rats. In addition, these drugs are associated with an increased incidence of osteochondrosis in rats as compared to the incidence observed in vehicle-treated rats (see WARNINGS). There is no evidence of arthropathies in fully mature dogs at intravenous doses up to 3 times the recommended maximum human dose (on a mg/m^2 basis or 5 times based on mg/kg basis), for a one-week exposure period.

Long-term, high-dose systemic use of other quinolones in experimental animals has caused lenticular opacities; however, this finding was not observed in any animal studies with ofloxacin.

Reduced serum globulin and protein levels were observed in animals treated with other quinolones. In one ofloxacin study, minor decreases in serum globulin and protein levels were noted in female cynomolgus monkeys dosed orally with 40 mg/kg ofloxacin daily for one year. These changes, however, were considered to be within normal limits for monkeys.

Crystalluria and ocular toxicity were not observed in any animals treated with ofloxacin.

REFERENCES

1. Clinical and Laboratory Standards Institute (CLSI). Methods for Dilution Antimicrobial Susceptibility Tests for Bacteria that Grow Aerobically; Approved Standard - Ninth Edition. CLSI document M07-A9,Clinical and Laboratory Standards Institute, 950 West Valley Road, Suite 2500, Wayne, Pennsylvania19087, USA, 2012.

2. Clinical and Laboratory Standards Institute (CLSI). Performance Standards for Antimicrobial Disk Diffusion Susceptibility Tests; Approved Standards – Eleventh Edition. CLSI document M02-A11,Clinical and Laboratory Standards Institute, 950 West Valley Road, Suite 2500, Wayne, Pennsylvania19087, USA, 2012.

3. Clinical and Laboratory Standards Institute (CLSI). Performance Standards for Antimicrobial Susceptibility Testing; Twenty-third Informational Supplement, CLSI document M100-S24, Clinical andLaboratory Standards Institute, 950 West Valley Road, Suite 2500, Wayne, Pennsylvania 19087,USA, 2014.

Manufactured By:

Cadila Pharmaceuticals Limited

1389, Dholka, District - Ahmedabad,

Gujarat State, INDIA

Manufactured for:
Modavar Pharmaceuticals LLC.
1016, 16th Street, Suite 602,
Washington, DC 20036
Toll free: 800 688 4697

Revised: October, 2024

Medication Guide

Ofloxacin Tablets, USP
(oh-FLOX-a-sin)

Rx only

Read the Medication Guide that comes with ofloxacin before you start taking it and each time you get a refill. There may be new information. This Medication Guide does not take the place of talking to your healthcare provider about your medical condition or your treatment.

What is the most important information I should know about ofloxacin tablets?

Ofloxacin belongs to a class of antibiotics called fluoroquinolones. Ofloxacin tablets can cause serious side effects. Some of these serious side effects can happen at the same time and could result in death. If you get any of the following serious side effects, get medical help right away. Talk with your healthcare provider about whether you should continue to take ofloxacin tablets.

1. Tendon rupture or swelling of the tendon (tendinitis).

- Tendon problems can happen in people of all ages who take ofloxacin tablets. Tendons are tough cords of tissue that connect muscles to bones.
  - Pain, swelling, tears, and inflammation of tendons including the back of the ankle (Achilles), shoulder, hand, or other tendon sites.
- The risk of getting tendon problems while you take ofloxacin tablets is higher if you:
  - are over 60 years of age
  - are taking steroids (corticosteroids)
  - have had a kidney, heart or lung transplant.
  - Tendon problems can happen in people who do not have the above risk factors when they take ofloxacin tablets. Other reasons that can increase your risk of tendon problems can include:
    - physical activity or exercise
    - kidney failure
    - tendon problems in the past, such as in people with rheumatoid arthritis (RA).
    - Stop taking ofloxacin immediately and get medical help right away at the first sign of tendon pain, swelling or inflammation. Stop taking ofloxacin tablets until tendinitis or tendon rupture has been ruled out by your healthcare provider. Avoid exercise and using the affected area. The most common area of pain and swelling is the Achilles tendon at the back of your ankle. This can also happen with other tendons.
    - Talk to your healthcare provider about the risk of tendon rupture with continued use of ofloxacin tablets. You may need a different antibiotic that is not a fluoroquinolone to treat your infection.
    - Tendon rupture can happen while you are taking or after you have finished taking ofloxacin tablets. Tendon ruptures have happened up to several months after patients have finished taking their fluoroquinolone.
    - Get medical help right away if you get any of the following signs or symptoms of a tendon rupture:
      - hear or feel a snap or pop in a tendon area
      - bruising right after an injury in a tendon area
      - unable to move the affected area or bear weight

2. Changes in sensation and possible nerve damage (Peripheral Neuropathy). Damage to the nerves in arms, hands, legs, or feet can happen in people who take fluoroquinolones, including ofloxacin. Stop taking ofloxacin immediately and talk to your healthcare provider right away if you get any of the following symptoms of peripheral neuropathy in your arms, hands, legs, or feet:

- pain
- burning
- tingling
- numbness
- weakness

The nerve damage may be permanent.

3. Central Nervous System (CNS) effects. Seizures have been reported in people who take fluoroquinolone antibacterial medicines, including ofloxacin. Tell your healthcare provider if you have a history of seizures before you start taking ofloxacin. CNS side effects may happen as soon as after taking the first dose of ofloxacin. Stop taking ofloxacin immediately and talk to your healthcare provider right away if you get any of these side effects, or other changes in mood or behavior:

- seizures
- hear voices, see things, or sense things that are not there (hallucinations)
- feel restless
- tremors
- feel anxious or nervous
- confusion
- depression
- trouble sleeping
- nightmares
- feel lightheaded or dizzy
- feel more suspicious (paranoia)
- suicidal thoughts or acts
- headaches that will not go away, with or without blurred vision

4. Worsening of myasthenia gravis (a disease that causes muscle weakness). Fluoroquinolones like ofloxacin tablets may cause worsening of myasthenia gravis symptoms, including muscle weakness and breathing problems. Call your healthcare provider right away if you have any worsening muscle weakness or breathing problems.

See the section "What are the possible side effects of ofloxacin tablets?" for more information about side effects.

What is ofloxacin?

Ofloxacin tablets are a fluoroquinolone antibiotic medicine used in adults to treat certain infections caused by certain germs called bacteria. It is not known if ofloxacin tablets are safe and work in people under 18 years of age. Children less than 18 years of age have a higher chance of getting bone, joint, or tendon (musculoskeletal) problems such as pain or swelling while taking ofloxacin tablets.

Sometimes infections are caused by viruses rather than by bacteria. Examples include viral infections in the sinuses and lungs, such as the common cold or flu. Antibiotics including ofloxacin tablets do not kill viruses.

Call your healthcare provider if you think your condition is not getting better while you are taking ofloxacin tablets.

Who should not take ofloxacin tablets?

Do not take ofloxacin tablets if you have ever had a severe allergic reaction to an antibiotic known as a fluoroquinolone, or if you are allergic to any of the ingredients in ofloxacin. Ask your healthcare provider if you are not sure. See the list of the ingredients in ofloxacin tablets at the end of this Medication Guide.

What should I tell my healthcare provider before taking ofloxacin tablets?

See "What is the most important information I should know about ofloxacin tablets?"

Tell your healthcare provider about all your medical conditions, including if you:

- have tendon problems-ofloxacin should not be used in patients who have a history of tendon problems
- have a disease that causes muscle weakness (myasthenia gravis)
- have central nervous system problems (such as epilepsy)
- have nerve problems-ofloxacin should not be used in patients who have a history of nerve problems called peripheral neuropathy
- have or anyone in your family has an irregular heartbeat, especially a condition called “QT prolongation.”
- have low blood potassium (hypokalemia)
- have a history of seizures
- have kidney problems. You may need a lower dose of ofloxacin tablets if your kidneys do not work well.
- have liver problems
- have rheumatoid arthritis (RA) or other history of joint problems
- are pregnant or planning to become pregnant. It is not known if ofloxacin tablets will harm your unborn child
- are breastfeeding or planning to breastfeed. Ofloxacin passes into breast milk. You and your healthcare provider should decide whether you will take ofloxacin tablets or breastfeed.

Tell your healthcare provider about all the medicines you take, including prescription and non-prescription medicines, vitamins, herbal and dietary supplements. Ofloxacin tablets and other medicines can affect each other causing side effects. Especially tell your healthcare provider if you take:

- an NSAID (Non-Steroidal Anti-Inflammatory Drug). Many common medicines for pain relief are NSAIDs. Taking an NSAID while you take ofloxacin tablets or other fluoroquinolones may increase your risk of central nervous system effects and seizures. See "What are the possible side effects of ofloxacin tablets"
- theophylline
- a blood thinner (warfarin, Coumadin®, Jantoven®)
- an oral anti-diabetes medicine or insulin
- a medicine to control your heart rate or rhythm (antiarrhythmics). See "What are the possible side effects of ofloxacin tablets?".
- an anti-psychotic medicine
- a tricyclic antidepressant
- a water pill (diuretic)
- a steroid medicine. Corticosteroids taken by mouth or by injection may increase the chance of tendon injury. See "What is the most important information I should know about ofloxacin tablets?".
- Certain medicines may keep ofloxacin tablets from working correctly. Take ofloxacin tablets either 2 hours before or 2 hours after taking these products:
  - an antacid, multivitamin, or other product that has magnesium, aluminum, iron, or zinc.
  - sucralfate (Carafate®)
  - didanosine (Videx®, Videx® EC)

Ask your healthcare provider if you are not sure if any of your medicines are listed above. Know the medicines you take. Keep a list of your medicines and show it to your healthcare provider and pharmacist when you get a new medicine.

How should I take ofloxacin tablets?

- Take ofloxacin tablets exactly as prescribed by your healthcare provider.
- Take ofloxacin tablets at about the same time each day.
- Drink plenty of fluids while taking ofloxacin tablets.
- Ofloxacin tablets can be taken with or without food.
- Do not skip any doses, or stop taking ofloxacin tablets , even if you begin to feel better, until you finish your prescribed treatment, unless:
  - you have tendon effects (see “What is the most important information I should know about ofloxacin tablets ?”),
  - you have nerve problems (see “What is the most important information I should know about ofloxacin tablets?”)
  - you have central nervous system problems (see “What is the most important information I should know about ofloxacin tablets?”)
  - you have a serious allergic reaction (see “What are the possible side effects of ofloxacin tablets ?”), or
  - your healthcare provider tells you to stop.

- This will help make sure that all of the bacteria are killed and lower the chance that the bacteria will become resistant to ofloxacin tablets. If this happens, ofloxacin tablets and other antibiotic medicines may not work in the future.
- If you miss a dose of ofloxacin tablets, take it as soon as you remember. Do not take two doses of ofloxacin tablets at the same time. Do not take more than two doses in one day.
- If you take too much, call your healthcare provider or get medical help immediately.

What should I avoid while taking ofloxacin tablets?

- Ofloxacin tablets can make you feel dizzy and lightheaded. Do not drive, operate machinery, or do other activities that require mental alertness or coordination until you know how ofloxacin tablets affect you.
- Avoid sunlamps, tanning beds, and try to limit your time in the sun. Ofloxacin tablets can make your skin sensitive to the sun (photosensitivity) and the light from sunlamps and tanning beds. You could get severe sunburn, blisters or swelling of your skin. If you get any of these symptoms while taking ofloxacin tablets, call your healthcare provider right away. You should use a sunscreen and wear a hat and clothes that cover your skin if you have to be in sunlight.

What are the possible side effects of ofloxacin tablets?

Ofloxacin tablets can cause side effects that may be serious or even cause death. See "What is the most important information I should know about ofloxacin tablets?"

Other serious side effects of ofloxacin tablets include:

- Serious allergic reactions.

Allergic reactions can happen in people taking fluoroquinolones, including ofloxacin tablets, even after only one dose. Stop taking ofloxacin tablets and get emergency medical help right away if you get any of the following symptoms of a severe allergic reaction:

-
  - hives
  - trouble breathing or swallowing
  - swelling of the lips, tongue, face
  - throat tightness, hoarseness
  - rapid heartbeat
  - faint
  - yellowing of the skin or eyes. Stop taking ofloxacin tablets and tell your healthcare provider right away if you get yellowing of your skin or white part of your eyes, or if you have dark urine. These can be signs of a serious reaction to ofloxacin tablets (a liver problem).
  - Aortic aneurysm and dissection
    Tell your healthcare provider if you have ever been told that you have an aortic aneurysm, a swelling of the large artery that carries blood from the heart to the body. Get emergency medical help right away if you have sudden chest, stomach, or back pain.

-
  - Skin rash

Skin rash may happen in people taking ofloxacin tablets, even after only one dose. Stop taking ofloxacin tablets at the first sign of a skin rash and call your healthcare provider. Skin rash may be a sign of a more serious reaction to ofloxacin.

- Intestine infection (Pseudomembranous colitis)

Pseudomembranous colitis can happen with most antibiotics, including ofloxacin tablets. Call your healthcare provider right away if you get watery diarrhea, diarrhea that does not go away, or bloody stools. You may have stomach cramps and a fever. Pseudomembranous colitis can happen 2 or more months after you have finished your antibiotic.

- Serious heart rhythm changes (QT prolongation and torsade de pointes)

Tell your healthcare provider right away if you have a change in your heart beat (a fast or irregular heartbeat), or if you faint. Ofloxacin tablets may cause a rare heart problem known as prolongation of the QT interval. This condition can cause an abnormal heartbeat and can be very dangerous. The chances of this happening are higher in people:

- who are elderly
- with a family history of prolonged QT interval
- with low blood potassium (hypokalemia)
- who take certain medicines to control heart rhythm (antiarrhythmics)
- Sensitivity to sunlight (photosensitivity): See "What should I avoid while taking ofloxacin tablets?"
- Low blood sugar (hypoglycemia). People who take ofloxacin tablets and other fluoroquinolone medicines with oral anti-diabetes medicines or with insulin can get low blood sugar (hypoglycemia). Follow your healthcare provider’s instructions for how often to check your blood sugar. If you have diabetes and you get low blood sugar while taking ofloxacin tablets, stop taking ofloxacin tablets right away and call your healthcare provider right away. Your antibiotic medicine may need to be changed.
- Changes in blood sugar
  People who take fluoroquinolone medicines with oral anti-diabetes medicines or with insulin can get low blood sugar (hypoglycemia) and high blood sugar (hyperglycemia). Follow your healthcare provider's instructions for how often to check your blood sugar. If you have diabetes and you get low blood sugar while taking ofloxacin, stop taking ofloxacin and call your healthcare provider right away. Your antibiotic medicine may need to be changed.

The most common side effects of ofloxacin tablets include:

- Sleep problems
- headache
- dizziness
- nausea
- vomiting
- diarrhea
- itching
- external genital itching in women
- vaginal inflammation (vaginitis)
- taste changes

Ofloxacin tablets may cause false-positive urine screening results for opiates when testing is done with some commercially available kits. A positive result should be confirmed using a more specific test.

These are not all the possible side effects of ofloxacin tablets. Tell your healthcare provider about any side effect that bothers you or that does not go away.

Call your doctor for medical advice about side effects. You may report side effects to FDA at 1-800-FDA-1088.

How should I store ofloxacin tablets?

- Store ofloxacin tablets at 20° to 25° C (68°F to 77°F).
- Keep the bottle that ofloxacin tablets come in closed tightly.
- Keep ofloxacin tablets and all medicines out of the reach of children.

General Information about ofloxacin tablets
Medicines are sometimes prescribed for purposes other than those listed in a Medication Guide.

Do not use ofloxacin tablets for a condition for which it is not prescribed.
Do not give ofloxacin tablets to other people, even if they have the same symptoms that you have. It may harm them.

This Medication Guide summarizes the most important information about ofloxacin tablets. If you would like more information about ofloxacin tablets, talk with your healthcare provider. You can ask your healthcare provider or pharmacist for information about ofloxacin tablets that is written for healthcare professionals. For more information go to www.modavar.com or call 800-688-4697.

What are the ingredients in ofloxacin tablets?

- Active ingredient: ofloxacin, USP
- Inactive ingredients: lactose monohydrate, pregelatinized maize starch, hydroxy propyl methyl cellulose, talc, magnesium stearate, polyethylene glycol, sodium starch glycolate and titanium dioxide. Additionally, the 200 mg and 400 mg tablets contain iron oxide yellow. The imprinting ink for 200 mg, 300 mg and 400 mg strength contains FD&C blue #1, isopropyl alcohol, N-butyl alcohol, propylene glycol, shellac and titanium dioxide.

This Medication Guide has been approved by the U.S.Food and Drug Administration.
All brand names listed are the registered trademarks of their respective owners and are not trademarks of Modavar Pharmaceuticals LLC.

Manufactured by:

Cadila Pharmaceuticals Limited
1389, Dholka, District - Ahmedabad,

Gujarat State, INDIA

Manufactured for:
Modavar Pharmaceuticals LLC.
1016, 16th Street, Suite 602,
Washington, DC 20036
Toll free: 800 688 4697

Revised: October, 2024

PACKAGE LABEL.PRINCIPAL DISPLAY PANEL

Ofloxacin Tablets, USP 200 mg 50s Label Text
NDC 72241-072-02
OFLOXACIN
TABLETS, USP
200 mg

PHARMACIST: PLEASE DISPENSE WITH

ATTACHED MEDICATION GUIDE

Rx only

50 TABLETS
Modavar Pharmaceuticals LLC.

Ofloxacin Tablets, USP 200 mg 100s Label Text
NDC 72241-072-05
OFLOXACIN
TABLETS, USP
200 mg

PHARMACIST: PLEASE DISPENSE WITH

ATTACHED MEDICATION GUIDE

Rx only

100 TABLETS
Modavar Pharmaceuticals LLC.

Ofloxacin Tablets, USP 200 mg 500s Label Text
NDC 72241-072-10
OFLOXACIN
TABLETS, USP
200 mg

PHARMACIST: PLEASE DISPENSE WITH

ATTACHED MEDICATION GUIDE

Rx only

500 TABLETS
Modavar Pharmaceuticals LLC.

Ofloxacin Tablets, USP 300 mg 50s Label Text

NDC 72241-073-02

OFLOXACIN

TABLETS, USP

300 mg

PHARMACIST: PLEASE DISPENSE WITH

ATTACHED MEDICATION GUIDE

Rx only

50 TABLETS

Modavar Pharmaceuticals LLC.

Ofloxacin Tablets, USP 300 mg 100s Label Text

NDC 72241-073-05

OFLOXACIN

TABLETS, USP

300 mg

PHARMACIST: PLEASE DISPENSE WITH

ATTACHED MEDICATION GUIDE

Rx only

100 TABLETS

Modavar Pharmaceuticals LLC.

Ofloxacin Tablets, USP 300 mg 500s Label Text

NDC 72241-073-10

OFLOXACIN

TABLETS, USP

300 mg

PHARMACIST: PLEASE DISPENSE WITH

ATTACHED MEDICATION GUIDE

Rx only

500 TABLETS

Modavar Pharmaceuticals LLC.

Ofloxacin Tablets, USP 400 mg 50s Label Text

NDC 72241-074-02

OFLOXACIN

TABLETS, USP

400 mg

PHARMACIST: PLEASE DISPENSE WITH

ATTACHED MEDICATION GUIDE

Rx only

50 TABLETS

Modavar Pharmaceuticals LLC.

Ofloxacin Tablets, USP 400 mg 100s Label Text

NDC 72241-074-05

OFLOXACIN

TABLETS, USP

400 mg

PHARMACIST: PLEASE DISPENSE WITH

ATTACHED MEDICATION GUIDE

Rx only

100 TABLETS

Modavar Pharmaceuticals LLC.

Ofloxacin Tablets, USP 400 mg 500s Label Text

NDC 72241-074-10

OFLOXACIN

TABLETS, USP

400 mg

PHARMACIST: PLEASE DISPENSE WITH

ATTACHED MEDICATION GUIDE

Rx only

500 TABLETS

Modavar Pharmaceuticals LLC.